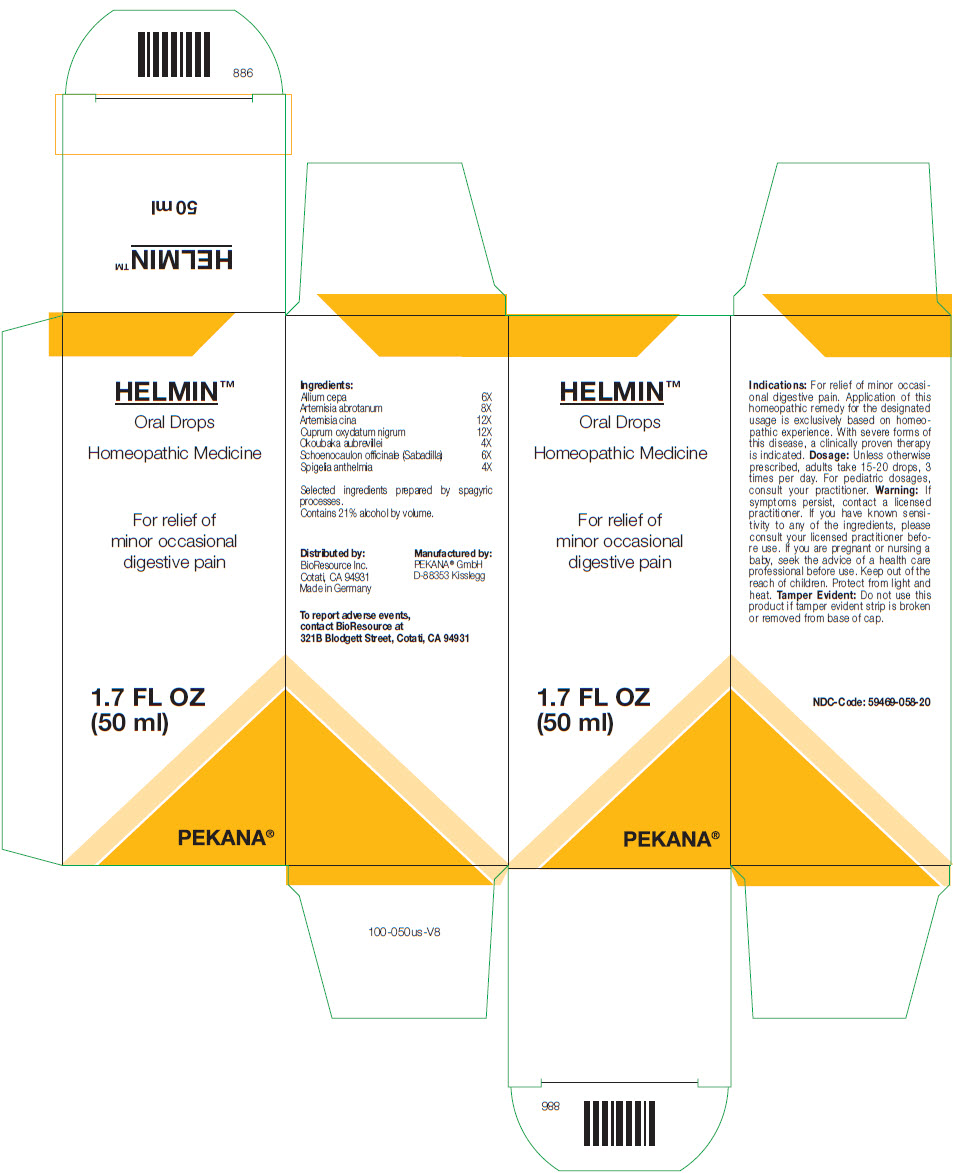 DRUG LABEL: HELMIN
NDC: 59469-058 | Form: SOLUTION/ DROPS
Manufacturer: PEKANA Naturheilmittel GmbH
Category: homeopathic | Type: HUMAN OTC DRUG LABEL
Date: 20221221

ACTIVE INGREDIENTS: Onion 6 [hp_X]/50 mL; Artemisia abrotanum Flowering Top 8 [hp_X]/50 mL; Artemisia cina Pre-Flowering Top 12 [hp_X]/50 mL; Cupric Oxide 12 [hp_X]/50 mL; Okoubaka aubrevillei Bark 4 [hp_X]/50 mL; Schoenocaulon officinale Seed 6 [hp_X]/50 mL; SPIGELIA ANTHELMIA WHOLE 4 [hp_X]/50 mL
INACTIVE INGREDIENTS: Water; Alcohol

HELMIN™

ACTIVE INGREDIENT

Ingredients:
Allium cepa | 6X
Artemisia abrotanum | 8X
Artemisia cina | 12X
Cuprum oxydatum nigrum | 12X
Okoubaka aubrevillei | 4X
Schoenocaulon officinale (Sabadilla) | 6X
Spigelia anthelmia | 4X

INACTIVE INGREDIENT

Selected ingredients prepared by spagyric processes.

Contains 21% alcohol by volume.

Indications

PURPOSE

For relief of minor occasional digestive pain. Application of this homeopathic remedy for the designated usage is exclusively based on homeopathic experience. With severe forms of this disease, a clinically proven therapy is indicated.

Dosage

Unless otherwise prescribed, adults take 15-20 drops, 3 times per day. For pediatric dosages, consult your practitioner.

Warning

ASK DOCTOR

If symptoms persist, contact a licensed practitioner. If you have known sensitivity to any of the ingredients, please consult your licensed practitioner before use. If you are pregnant or nursing a baby, seek the advice of a health care professional before use.

Keep out of the reach of children.

STORAGE AND HANDLING

Protect from light and heat.

Tamper Evident

Do not use this product if tamper evident strip is broken or removed from base of cap.

QUESTIONS

To report adverse events, contact BioResource at 321B Blodgett Street, Cotati, CA 94931

Manufactured by:
PEKANA® GmbH
D-88353 Kisslegg

Distributed by:
BioResource Inc.
Cotati, CA 94931

PRINCIPAL DISPLAY PANEL - 50 ml Bottle Box

HELMIN™
Oral Drops

Homeopathic Medicine

For relief of
minor occasional
digestive pain

1.7 FL OZ
(50 ml)

PEKANA®